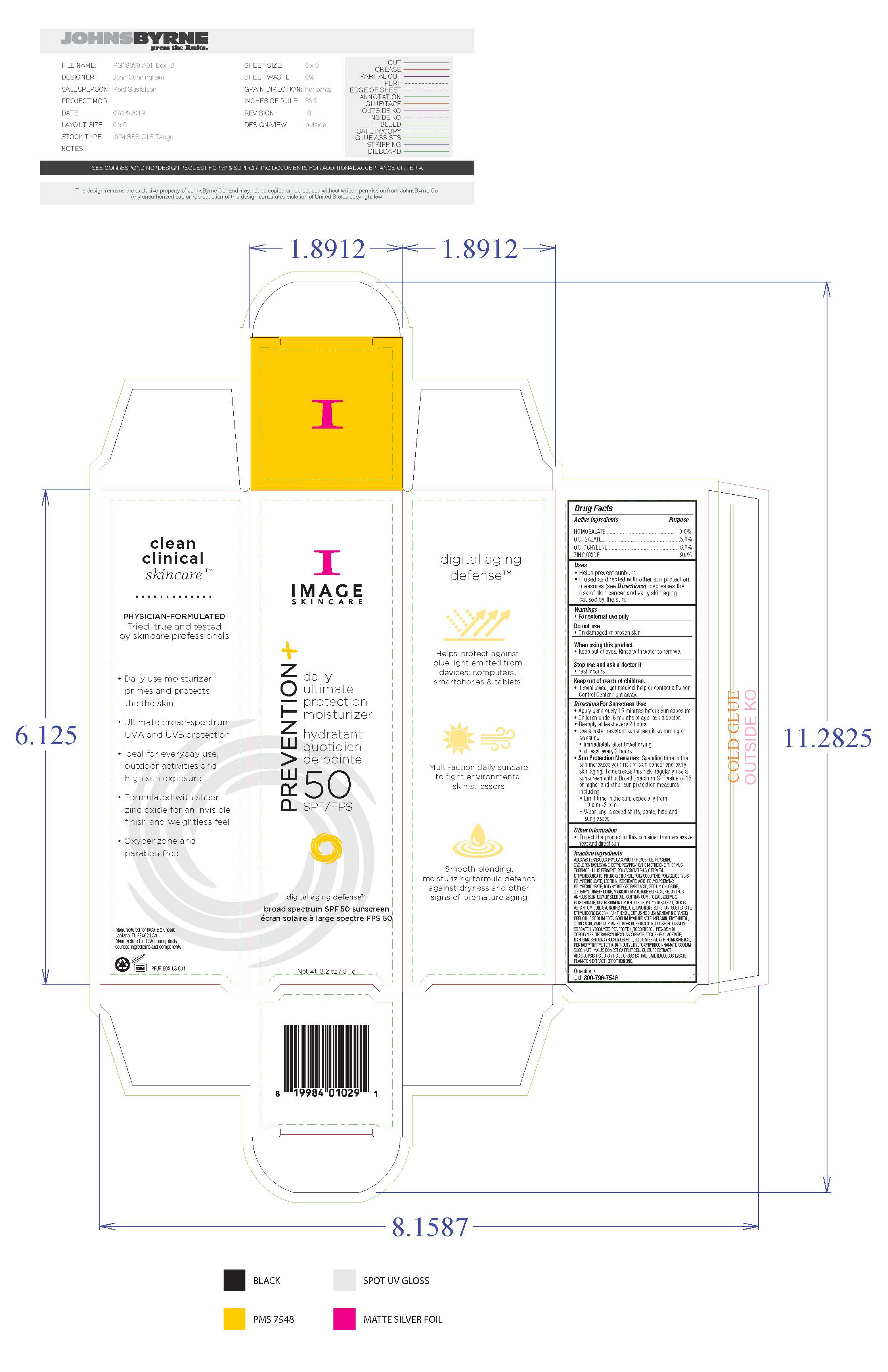 DRUG LABEL: Image Skincare Prevention Plus Daily Ultimate Protection
NDC: 60232-1022 | Form: CREAM
Manufacturer: Swiss-American CDMO, LLC
Category: otc | Type: HUMAN OTC DRUG LABEL
Date: 20231106

ACTIVE INGREDIENTS: HOMOSALATE 100 g/1000 g; OCTISALATE 50 g/1000 g; OCTOCRYLENE 60 g/1000 g; ZINC OXIDE 90 g/1000 g
INACTIVE INGREDIENTS: WATER; PANTHENOL; EDETATE DISODIUM; GLYCERIN; SODIUM CHLORIDE; XANTHAN GUM; HYALURONIC ACID; PHENOXYETHANOL; ETHYLHEXYLGLYCERIN; ERGOTHIONEINE; ERYTHRITOL; HOMARINE HYDROCHLORIDE; CYCLOMETHICONE 5; .ALPHA.-TOCOPHEROL ACETATE; TETRAHEXYLDECYL ASCORBATE; PEG-8/SMDI COPOLYMER; MALUS DOMESTICA WHOLE; LECITHIN, SOYBEAN; MICROCOCCUS LUTEUS; ARABIDOPSIS THALIANA; MARRUBIUM VULGARE; ANHYDROUS CITRIC ACID; POTASSIUM SORBATE; THERMUS THERMOPHILUS; DISTEARDIMONIUM HECTORITE; POLYGLYCERYL-2 ISOSTEARATE; .DELTA.-TOCOPHEROL; CETYL PEG/PPG-10/1 DIMETHICONE (HLB 1.5); MEDIUM-CHAIN TRIGLYCERIDES; POLYHYDROXYSTEARIC ACID (2300 MW); ISOSTEARIC ACID; SUNFLOWER OIL; ORANGE OIL; VANILLA BEAN; AGATHOSMA BETULINA LEAF OIL; SODIUM SUCCINATE ANHYDROUS; POLYSORBATE 20; POLYISOBUTYLENE (1000 MW); CETEARYL ETHYLHEXANOATE; LIMONENE, (+/-)-

Image Skincare Prevention Plus Daily Ultimate Protection

Warnings

For external use only. Do not use on damaged or broken skin. When using this product keep out of eyes. Rinse with water to remove. Stop use and ask a doctor if rash occurs. If swallowed, get medical help or contact a Poison Control Center right away.

Keep out of Reach of Children

Active Ingredients

Homosalate 10.0% Sunscreen

Octisalate 5.0% Sunscreen

Octocrylene 6.0% Sunscreen

Zinc Oxide 9.0% Sunscreen

Uses

Helps prevent sunburn. If used as directed with other sun protection measures (see Directions), decreases the risk of skin cancer and early skin aging caused by the sun.

Uses

Helps prevent sunburn. If used as directed with other sun protection measures (see Directions), decreases the risk of skin cancer and early skin aging caused by the sun.

Directions for Sunscreen Use

Apply generously 15 minutes before sun exposure. Children under 6 months of age: ask a doctor. Reapply at least every 2 hours. Use a water resistant sunscreen if swimming or sweating. Immediately after towel drying. At least every 2 hours. Sun Protection Measures. Spending time in the sun increases your risk of skin cancer and early skin aging. To decrease this risk, regularly use a sunscreen with a Broad Spectrum SPF value of 15 or higher and other sun protection measures including: limit time in the sun, especially from 10am to 2pm, wear long-sleeved shirts, pants, hats and sunglasses.

Other Information

Protect the product in this container from excessive heat and direct sun.

Inactive Ingredients

water, caprylic/capric triglyceride, glycerin, cyclopentasiloxane, cetyl PEG/PPG-10/1 dimethicone, thermus thermophillus ferment, polyacrylate-13, cetearyl ethylhexanoate, phenoxyethanol, polyisobutene, polyglyceryl-6 polyricinoleate, lecithin, isostearic acid, polyglyceryl-3 polyricinoleate, polyhydroxystearic acid, soidum chloride, cetearyl dimethicone, marrubium vulgare extract, helianthus annus (sunflower) see oil, disteardimonium hectorite, polysorbate 20, citrus aurantum dulcis (orange) peel oil, limonene, sorbitan isostearate, ethylhexylglycerin, panthenol, citrus nobils (mandarin orange) peel oil, disodium EDTA, sodium hyaluronate, melanin, erythritol, citric acid, vanilla planifolia fruit extract, glycose, potassium sorbate, hydrolyzed pea protein, tocopherol, PEG-8/SMDI copolymer, tetrahexyldecyl ascoorbate, tocopheryl acetate, barosma betuuna (buchu) leaf oil, soidum benzoate, homarine HCL, pentaerythrityl tetra-di-t-butylhydroxyhydrocinnamate, sodium succinate, mallis domestica fruit cell culture extract, arabidopsis thaliana (thale cress) extract, micrococcus lysate, plankton extract, ergothioneine

Questions

Call 800-796-7546